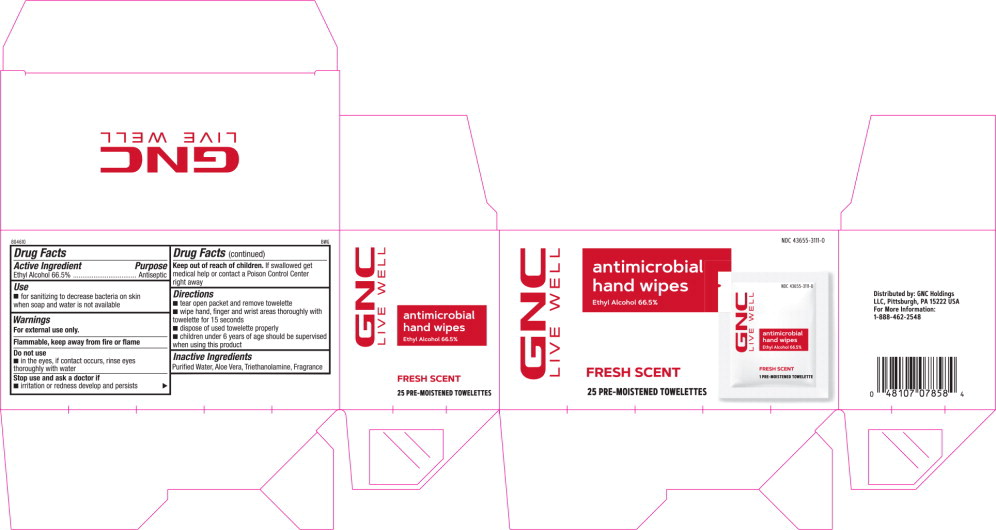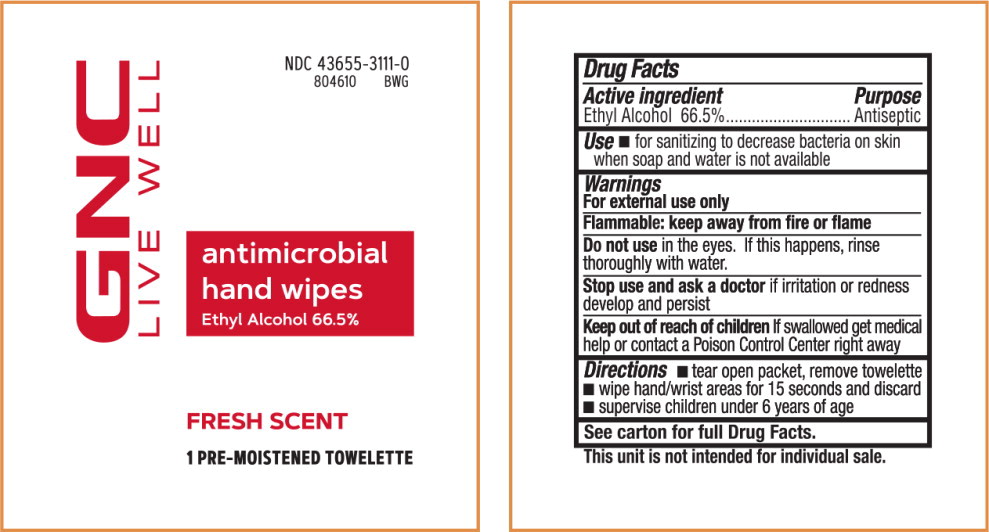 DRUG LABEL: GNC Antimicrobial Hand Wipes
NDC: 43655-3111 | Form: CLOTH
Manufacturer: GNC Holdings LLC
Category: otc | Type: HUMAN OTC DRUG LABEL
Date: 20230131

ACTIVE INGREDIENTS: ALCOHOL 66.5 mL/100 mL
INACTIVE INGREDIENTS: ALOE VERA LEAF; WATER; TROLAMINE

Drug Facts

Active Ingredient

Ethyl Alcohol 66.5%

Purpose

Antiseptic

Use

- for sanitizing to decrease bacteria on skin when soap and water is not available

Warnings

For external use only.

Flammable, keep away from fire or flame

Do not use

- in the eyes, if contact occurs, rinse eyes thoroughly with water

Stop use and ask a doctor if

- irritation or redness develop and persists

Keep out of reach of children. If swallowed get medical help or contact a Poison Control Center right away

Directions

- tear open packet and remove towelette
- wipe hand, finger and wrist areas thoroughly with towelette for 15 seconds
- dispose of used towelette properly
- children under 6 years of age should be supervised when using this product

Inactive Ingredients

Purified Water, Aloe Vera, Triethanolamine, Fragrance

Principal Display Panel – Carton Label

NDC 43655-3111-0

GNC
LIVE WELL

Antimicrobial
hand wipes

Ethyl Alcohol 66.5%

FRESH SCENT

25 PRE-MOISTENED TOWELETTES

Principal Display Panel – Pouch Label

NDC 43655-3111-0

GNC
LIVE WELL

Antimicrobial
hand wipes

Ethyl Alcohol 66.5%

FRESH SCENT

1 PRE-MOISTENED TOWELETTE